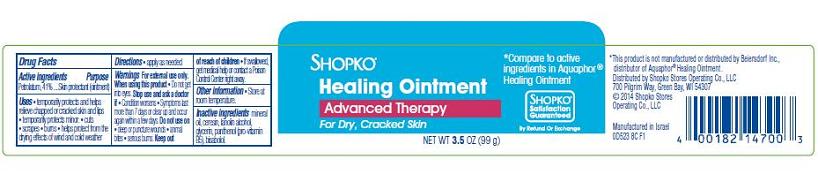 DRUG LABEL: Shopko Healing
NDC: 37012-523 | Form: OINTMENT
Manufacturer: Shopko Stores Operating Co., LLC
Category: otc | Type: HUMAN OTC DRUG LABEL
Date: 20140408

ACTIVE INGREDIENTS: PETROLATUM 41 g/100 g
INACTIVE INGREDIENTS: MINERAL OIL; CERESIN; LANOLIN ALCOHOLS; GLYCERIN; PANTHENOL; LEVOMENOL

SHOPKO® Healing Ointment

Active ingredient

Petrolatum, 41%

Purpose

Skin Protectant (ointment)

Uses

- temporarily protects and helps relieve chapped or cracked skin and lips
- temporarily protects minor:
- cuts
- scrapes
- burns
- helps protect from the drying effects of wind and cold weather

Directions

- apply as needed

Warnings

For external use only.

When using this product

- Do not get into eyes.

Stop use and ask a doctor if

- Condition worsens
- Symptoms last more than 7 days or clear up and occur again within a few days.

Do not use on

- deep or puncture wounds
- animal bites
- serious burns

Keep out of reach of children

- If swallowed, get medical help or contact a Poison Control Center right away.

Other information

- Store at room temperature.

Inactive ingredients

mineral oil, ceresin, lanolin alcohol, glycerin, panthenol (pro-vitamin B5), bisabolol.

Package/Label Principal Display Panel - Carton Label

SHOPKO®

Healing Ointment
Advanced Therapy
For Dry, Cracked Skin

NET WT 3.5 OZ (99 g)

*Compare to active ingredients of Aquaphor® Healing Ointment

SHOPKO®
Satisfaction Guaranteed

By Refund or Exchange

*This product is not manufactured or distributed by Beiersdorf, Inc., distributor of Aquaphor® Healing Ointment.

Distributed by Shopko Stores Operating Co., LLC
700 Pilgrim Way, Green Bay, WI 54307
©2014 Shopko Stores
Operating Co., LLC

Manufactured in Israel
0D523 8C F1

Carton Label